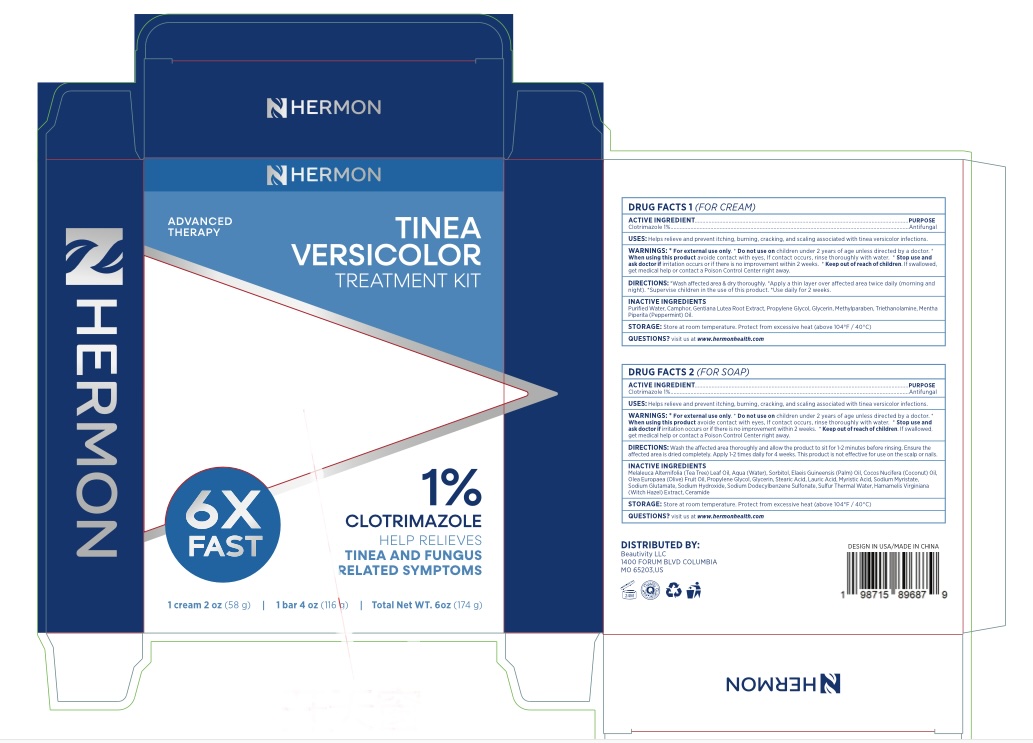 DRUG LABEL: Tinea Versicolor Treatment Kit
NDC: 85398-004 | Form: KIT | Route: TOPICAL
Manufacturer: Beautivity LLC
Category: otc | Type: HUMAN OTC DRUG LABEL
Date: 20260302

ACTIVE INGREDIENTS: CLOTRIMAZOLE 10 mg/1 g; CLOTRIMAZOLE 1 g/100 g
INACTIVE INGREDIENTS: PROPYLENE GLYCOL; GLYCERIN; METHYLPARABEN; PEPPERMINT OIL; WATER; GENTIANA LUTEA ROOT; CAMPHOR (SYNTHETIC); TROLAMINE; PROPYLENE GLYCOL; SODIUM HYDROXIDE; HAMAMELIS VIRGINIANA ROOT BARK/STEM BARK; OLEA EUROPAEA (OLIVE) FRUIT OIL; SODIUM DODECYLBENZENESULFONATE; SODIUM MYRISTATE; GLYCERIN; SODIUM GLUTAMATE; ELAEIS GUINEENSIS (PALM) OIL; CERAMIDE NP; SORBITOL; COCOS NUCIFERA (COCONUT) OIL; WATER; MELALEUCA ALTERNIFOLIA (TEA TREE) LEAF OIL; MYRISTIC ACID; STEARIC ACID; LAURIC ACID; SULFUR

Update-85398-004-01

ACTIVE INGREDIENT

Cream: Clotrimazole 1%
Soap bar: Clotrimazole 1%

PURPOSE

Antifungal

INDICATIONS AND USAGE

Helps relieve and prevent itching, burning, cracking, and scaling associated with tinea versicolor infections.

WARNINGS

For external use only

Do not use on children under 2 years of age unless directed by a doctor.

When using this product avoid contact with eyes, If contact occurs, rinse thoroughly with water.

Stop use and ask doctor if irritation occurs or if there is no improvement within 2 weeks.

keep out of reach of children. If swallowed, get medical help or contact a Posion Control enter right away.

DOSAGE AND ADMINISTRATION

Wash the affected area & dry thoroughly.
Apply a thin layer over affected area twice daily (morning and night).
Supervise children in the use of this produt.
Use daily for 2 weeks.

INACTIVE INGREDIENT

Cream: Purified Water, Camphor, Gentiana Lutea Root, Propylene Glycol, Glycerin, Methylparaben, Triethanolamine, Peppermint Oil
Soap Bar: Melaleuca Alternifolia (Tea Tree) Leaf Oil, Water, Sorbitol, Elaeis Guineensis (Palm) Oil, Cocos Nucifera (Coconut) Oil, Olea Europaea (Olive) Fruit Oil, Propylene Glycol, Glycerin, Stearic Acid, Lauric Acid, Myristic Acid, Sodium Myristate, Sodium Glutamate, Sodium Hydroxide, Sodium Dodecylbenzenesulfonate, Sulfur, Hamamelis Virginiana Root Bark, Ceramide NP

STORAGE AND HANDLING

Store at room temperature. Protect from excessive heat (above 104ºF / 40ºC)

QUESTIONS

visit us at www.hermonhealth.com